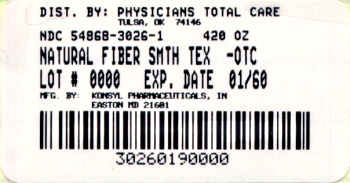 DRUG LABEL: Natural Fiber Powder
NDC: 54868-3026 | Form: GRANULE
Manufacturer: Physicians Total Care, Inc.
Category: otc | Type: HUMAN OTC DRUG LABEL
Date: 20120124

ACTIVE INGREDIENTS: PSYLLIUM HUSK 3.4 g/100 g
INACTIVE INGREDIENTS: CITRIC ACID MONOHYDRATE; D&C YELLOW NO. 10; FD&C YELLOW NO. 6; SUCROSE

Active ingredient (in each dose)
Psyllium Hydrophilic Mucilloid 3.4 grams

Purpose

Bulk-Forming Laxative

INDICATIONS AND USAGE

Use For relief of occasional constipation. Generally produces effect in 12-72 hours. Naural bulk producing fiber encourages normal elimination without chemical stimulants.

WARNINGS

Warnings Allergy alert Inhaled or ingested psyllium powder may cause an allergic reaction in people sensitive to psyllium. Choking Taking this product without adequate fluid may cause it ot swell and block your throat or esophagus and may cause choking. Do not take this product if you have difficulty in swallowing. If you experience chest pain, vomiting or difficulty in swallowing or breathing after taking this product, seek immediate medical attention.

Do not use laxative products when abdominal pain, nausea or vomiting are present unless directed by a doctor.

Ask a doctor before use if you have - a sudden change in bowel habits that persists over a period of two weeks.

When using this product - do not take for a period longer than 1 week, unless directed by a doctor

Stop use and ask a doctor if - you experience rectal bleeding - you fail to have a bowel movement

Keep out of reach of children. In case of overdose, get medical help or contact a Poison Control Center right away.

DOSAGE AND ADMINISTRATION

Directions Mix this product (child or adult dose) with at least 8 ounces (a full glass) of water or other fluid. Taking this product without enough liquid may cause choking. See choking warnings. Adults and children 12 years and over: sprinkle one dose, 1 rounded tablespoonful (12g), in 8 oz of liquid, 1-3 times daily. Children 6 years to under 12 years: 1/2 the adult dose in 8 oz of liquid, up to 3 times daily. Children under 6 years: Consult a doctor.

Other information - each 12 g dose contains: Calcium 6 mg, Potassium 31 mg, Sodium 3 mg - store below 86 Degree F (30 Degree Centigrade) - keep container tightly closed - protect from excessive moisture - tamper-evident bottle mouth sealed for your protection - do not use if imprinted inner seal is broken or missing - laxatives, including bulk fibers, may affect how other medicines work, wait 1-2 hours before or after taking other medicines. - can be taken 1 to 3 times daily, before or after meals, mornings, or evenings - maximum daily dose (3 tablespoonfuls) is very low sodium - do not discard Konsyl Orange powder into any plumbing systems - note to diabetics: this product contains 66% sugar (sucrose) - each dose provides 3 grams total dietary fiber - each dose contains 35 calories

INACTIVE INGREDIENT

Inactive ingredients citric acid, D and C yellow No. 10 and FD and C Yellow No.6 (Sunset Yellow), flavoring, sucrose.

QUESTIONS

Questions? Call Konsyl Pharmaceuticals, Inc. at 1-800-36-6795 8:30 a.m to 5 p.m. ET.

When using this product physicians recommend a gradual increase in dietary fiber. If minor gas or bloating occurs, begin with a increase the dose over several days. Always follow with 8 oz. of fluid. Manufactured by Konsyl Pharmaceuticals, Inc. Easton, MD 21601 www.konsyl.com Konsyl Pharmaceuticals, Inc. 33792 0810 Dietary Fiber Supplement Diets low in saturated fat and cholesterol that include 7 grams of soluble fiber per day from psyllium hust may reduce the risk of Coronary Heart Disease (CHD) by lowering cholesterol. ONE ADULT DOSE OF THIS PRODUCT CONTAINS 2.0 GRAMS PF THIS SOLUBLE FIBER = 3.4 G OF PSYLLIUM Dosage Adults 12 years and older: 1 Rounded teaspoonful in 8 oz. of fluid 2 TIMES DAILY, follow with additional fluid to aid product action, before or after meals, mornings or evenings. Children under 12 years: Consult a doctor. Notice Ask a doctor before use if you consider taking this product as part of a cholesterol-lowering program. See directions for use before taking this product. Supplements Facts Serving size (dose): 1 rounded teaspoonful psyllium 3.4g Serving per container 45 Amount Per Serving %DV* Calories (Available) 35 Sodium 0% Carbohydrates (Available) 8g 3% Dietary Fiber 3g 11% Soluble Fiber 2g - Sugars 8g - Calcium 0% Iron 6% *Percent Daily Values (DV) are based on a 2,000 calorie diet. - Daily Value (DV) not established.

PACKAGE LABEL

Psyllium Hydrophilic Mucilloid Smooth Texture Gluten Free Helps Lower Cholesterol NET WEIGHT 12.0g K PAREVE SUPPLEMENTS / LAXATIVE TAMPER-EVIDENT PACKAGE. DO NOT USE IF OPENED OR DAMAGED. DIRECTIONS FOR USE: MIX THIS PRODUCT (CHILD OF ADULT DOSE) WITH AT LEAST 8 OUNCES (A FULL GLASS) OF WATER OR OTHER FLUID/ TAKING THIS PRODUCT WITHOUT ENOUGH LIQUID MAY CAUSE CHOKING. SEE WARNINGS. 1. Sprinkle one packet into a shaker or glass containing 8 oz. of cool water. 2 Cover. Shake well for 3-5 seconds, or stir well. 3. Drink promptly. If mixture thickens, add more liquid and stir. Follow with additional liquid to aid product action. DOSAGE: Adults and children 12 years of age and over: One packet (or dose) 1 to 3 times daily, before or after meals, or as directed by a doctor. Children 6 to under 12 years of age: 1/2 adult dose, or as directed by a doctor. Children under 6 years of age: Consult a doctor. INDICATIONS: For relief of occasional constipation (irregularity). This product generally produces bowel movement in 12 to 72 hours. See insert or carton for complete WARNINGS. ALLERGY ALERT: Inhaled or ingested psyllium powder may cause an allergic reaction in people sensitive to psyllium.

Manufactured by Konsyl Pharmaceuticals, Inc. Easton, MD 21601 Store below 86 Degree F (30 Degree Centigrade) 3 02241 85200 5

Additional barcode labeling by: Physicians Total Care, Inc., Tulsa, Oklahoma 74146

PACKAGE LABEL

NDC 54868-3026-1

Natural Fiber Smooth Texture Powder

Psyllium Hydrophilic Mucilloid Heart Healthy Smooth Texture

Gluten Free Helps Lower Cholesterol

K PAREVE Naturally Sweetened SUPPLEMENTS / LAXATIVE

NET WEIGHT 538 (19oz)

(FILL CONTROLLED BY WEIGHT NOT VOLUME)